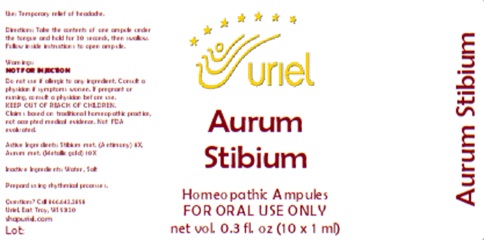 DRUG LABEL: Aurum Stibium
NDC: 48951-1346 | Form: LIQUID
Manufacturer: Uriel Pharmacy Inc.
Category: homeopathic | Type: HUMAN OTC DRUG LABEL
Date: 20260116

ACTIVE INGREDIENTS: ANTIMONY 8 [hp_X]/1 mL; GOLD 10 [hp_X]/1 mL
INACTIVE INGREDIENTS: SODIUM CHLORIDE; WATER

Aurum Stibium

PURPOSE

Use: Temporary relief of headache.

INDICATIONS AND USAGE

FOR ORAL USE ONLY

DOSAGE AND ADMINISTRATION

Directions: Take the contents of one ampule under the tongue and hold for 30 seconds, then swallow. Follow inside instructions to open ampule.

Warnings:
NOT FOR INJECTION
Do not use if allergic to any ingredient. Consult a physician if symptoms worsen. If pregnant or nursing, consult a physician before use.
Claims based on traditional homeopathic practice, not accepted medical evidence. Not FDA evaluated.

KEEP OUT OF REACH OF CHILDREN.

ACTIVE INGREDIENT

Active Ingredients: Stibium met. (Antimony) 8X, Aurum met. (Metallic gold) 10X

Inactive Ingredients: Water, Salt

Prepard using rhythmical processes.

Questions? Call 866.642.2858
Uriel, East Troy, WI 53120
shopuriel.com

Lot: